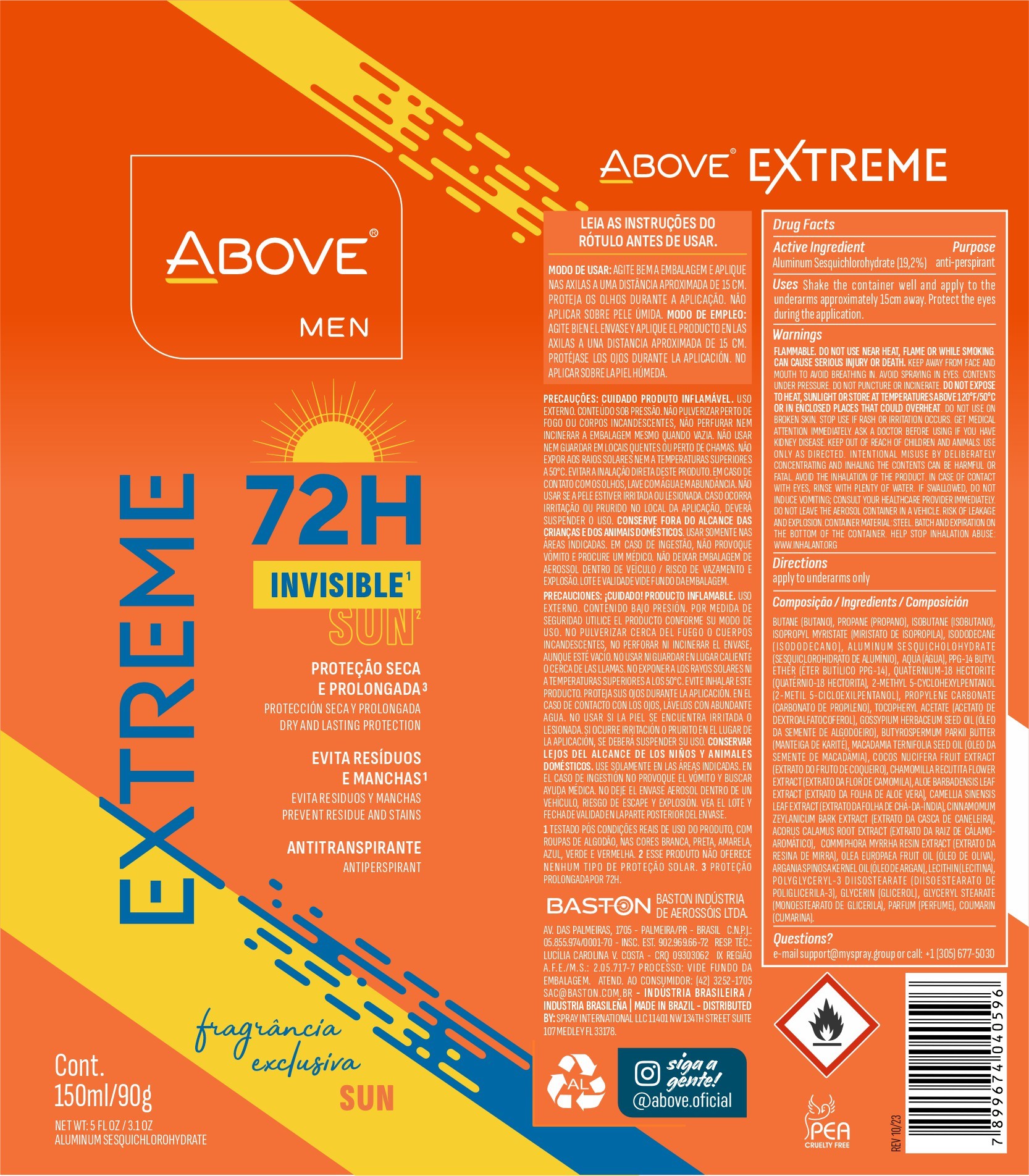 DRUG LABEL: ANTIPERSPIRANT ABOVE EXTREME SUN MEN				
NDC: 73306-1162 | Form: AEROSOL, SPRAY
Manufacturer: BASTON INDUSTRIA DE AEROSSOIS LTDA
Category: otc | Type: HUMAN OTC DRUG LABEL
Date: 20240709

ACTIVE INGREDIENTS: ALUMINUM SESQUICHLOROHYDRATE 19 mg/90 g
INACTIVE INGREDIENTS: ISOBUTANE

ANTIPERSPIRANT ABOVE EXTREME SUN MEN

ACTIVE INGREDIENT

ALUMINUM SESQUICHOLOHYDRATE 19.2 %

INACTIVE INGREDIENT

BUTANE (BUTANO) 56.55
PROPANE (PROPANO) 17.4
ISOBUTANE (ISOBUTANO) 13.05
ISOPROPYL MYRISTATE (MIRISTATO DE ISOPROPILA) 3.4125
ISODODECANE (ISODODECANO) 3.1785
PPG-14 BUTYL ETHER (ÉTER BUTÍLICO PPG-14) 0.7802015
PARFUM (PERFUME) 0.78
QUATERNIUM-18 HECTORITE (QUATÉRNIO-18 HECTORITA) 0.364
2-METHYL 5-CYCLOHEXYLPENTANOL (2-METIL 5-CICLOEXILPENTANOL) 0.26
PROPYLENE CARBONATE (CARBONATO DE PROPILENO) 0.195
TOCOPHERYL ACETATE (ACETATO DE DEXTROALFATOCOFEROL) 0.026
GOSSYPIUM HERBACEUM SEED OIL (ÓLEO DA SEMENTE DE ALGODOEIRO) 0.0039533
BUTYROSPERMUM PARKII BUTTER (MANTEIGA DE KARITÉ) 0.000715
MACADAMIA TERNIFOLIA SEED OIL (ÓLEO DA SEMENTE DE MACADÂMIA) 0.000715
COCOS NUCIFERA FRUIT EXTRACT (EXTRATO DO FRUTO DE COQUEIRO) 0.000715
CHAMOMILLA RECUTITA FLOWER EXTRACT (EXTRATO DA FLOR DE CAMOMILA) 0.000715
ALOE BARBADENSIS LEAF EXTRACT (EXTRATO DA FOLHA DE ALOE VERA) 0.000715
CAMELLIA SINENSIS LEAF EXTRACT (EXTRATO DA FOLHA DE CHÁ-DA-ÍNDIA) 0.000715
CINNAMOMUM ZEYLANICUM BARK EXTRACT (EXTRATO DA CASCA DE CANELEIRA) 0.000715
ACORUS CALAMUS ROOT EXTRACT (EXTRATO DA RAIZ DE CÁLAMO-AROMÁTICO) 0.000715
COMMIPHORA MYRRHA RESIN EXTRACT (EXTRATO DA RESINA DE MIRRA) 0.000715
OLEA EUROPAEA FRUIT OIL (ÓLEO DE OLIVA) 0.000715
ARGANIA SPINOSA KERNEL OIL (ÓLEO DE ARGAN) 0.00039
LECITHIN (LECITINA) 0.0003263
POLYGLYCERYL-3 DIISOSTEARATE (DIISOESTEARATO DE POLIGLICERILA-3) 0.0003263
GLYCERIN (GLICEROL) 0.0003263
GLYCERYL STEARATE (MONOESTEARATO DE GLICERILA) 0.0003263

PURPOSE

ANTIPERSPIRANT

INDICATIONS AND USAGE

Shake the container well and apply to the
underarms approximately 15cm away. Protect the eyes
during the application

WARNINGS AND PRECAUTIONS SECTION]
FLAMMABLE. DO NOT USE NEAR HEAT, FLAME OR WHILE SMOKING.
CAN CAUSE SERIOUS INJURY OR DEATH. KEEP AWAY FROM FACE AND
MOUTH TO AVOID BREATHING IN. AVOID SPRAYING IN EYES. CONTENTS
UNDER PRESSURE. DO NOT PUNCTURE OR INCINERATE. DO NOT EXPOSE
TO HEAT, SUNLIGHT OR STORE AT TEMPERATURES ABOVE 120°F/50°C
OR IN ENCLOSED PLACES THAT COULD OVERHEAT. DO NOT USE ON
BROKEN SKIN. STOP USE IF RASH OR IRRITATION OCCURS. GET MEDICAL
ATTENTION IMMEDIATELY. ASK A DOCTOR BEFORE USING IF YOU HAVE
KIDNEY DISEASE. KEEP OUT OF REACH OF CHILDREN AND ANIMALS. USE
ONLY AS DIRECTED. INTENTIONAL MISUSE BY DELIBERATELY
CONCENTRATING AND INHALING THE CONTENTS CAN BE HARMFUL OR
FATAL. AVOID THE INHALATION OF THE PRODUCT. IN CASE OF CONTACT
WITH EYES, RINSE WITH PLENTY OF WATER. IF SWALLOWED, DO NOT
INDUCE VOMITING; CONSULT YOUR HEALTHCARE PROVIDER IMMEDIATELY.
DO NOT LEAVE THE AEROSOL CONTAINER IN A VEHICLE. RISK OF LEAKAGE
AND EXPLOSION. CONTAINER MATERIAL: STEEL. BATCH AND EXPIRATION ON
THE BOTTOM OF THE CONTAINER. HELP STOP INHALATION ABUSE:
WWW.INHALANT.ORG

KEEP OUT OF REACH OF CHILDREN

DOSAGE AND ADMINISTRATION

Shake the container well and apply to the
underarms approximately 15cm away. Protect the eyes
during the application

QUESTIONS

MAIL : SUPPORT@MYSPRAY.GROUP OR CALL (305) 677-5030

WARNINGS

FLAMMABLE. DO NOT USE NEAR HEAT, FLAME OR WHILE SMOKING.
CAN CAUSE SERIOUS INJURY OR DEATH. KEEP AWAY FROM FACE AND
MOUTH TO AVOID BREATHING IN. AVOID SPRAYING IN EYES. CONTENTS
UNDER PRESSURE. DO NOT PUNCTURE OR INCINERATE. DO NOT EXPOSE
TO HEAT, SUNLIGHT OR STORE AT TEMPERATURES ABOVE 120°F/50°C
OR IN ENCLOSED PLACES THAT COULD OVERHEAT. DO NOT USE ON
BROKEN SKIN. STOP USE IF RASH OR IRRITATION OCCURS. GET MEDICAL
ATTENTION IMMEDIATELY. ASK A DOCTOR BEFORE USING IF YOU HAVE
KIDNEY DISEASE. KEEP OUT OF REACH OF CHILDREN AND ANIMALS. USE
ONLY AS DIRECTED. INTENTIONAL MISUSE BY DELIBERATELY
CONCENTRATING AND INHALING THE CONTENTS CAN BE HARMFUL OR
FATAL. AVOID THE INHALATION OF THE PRODUCT. IN CASE OF CONTACT
WITH EYES, RINSE WITH PLENTY OF WATER. IF SWALLOWED, DO NOT
INDUCE VOMITING; CONSULT YOUR HEALTHCARE PROVIDER IMMEDIATELY.
DO NOT LEAVE THE AEROSOL CONTAINER IN A VEHICLE. RISK OF LEAKAGE
AND EXPLOSION. CONTAINER MATERIAL: STEEL. BATCH AND EXPIRATION ON
THE BOTTOM OF THE CONTAINER. HELP STOP INHALATION ABUSE:
WWW.INHALANT.ORG